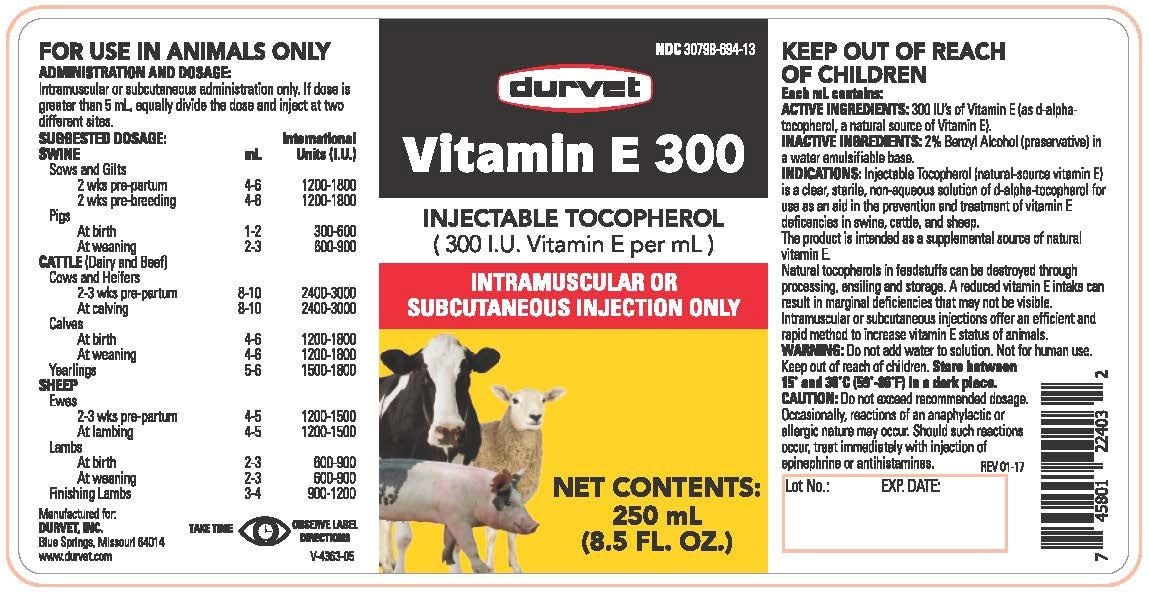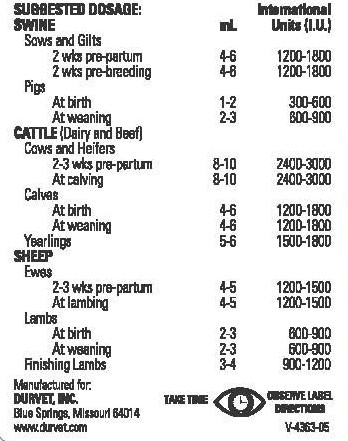 DRUG LABEL: Vitamin E 300
NDC: 30798-694 | Form: INJECTION
Manufacturer: Durvet, Inc.
Category: animal | Type: OTC ANIMAL DRUG LABEL
Date: 20231208

ACTIVE INGREDIENTS: ALPHA-TOCOPHEROL 300 mg/300 mL

Vitamin E 300

DOSAGE AND ADMINISTRATION

INJECTABLE TOCOPHEROL

(300 I.U. Vitamin E per mL)

FOR USE IN ANIMALS ONLY

Dosage and Administration:
Intramuscular or subcutaneous administration only. May be repeated as needed. If dose is greater than 5 mL, equally divide the dose and inject at two different sites.

INDICATIONS

Vitamin E-300 Injectable Tocopherol (natural-source vitamin E) is a clear, sterile, water emulsifiable solution of d-alpha-tocopherol for use as an aid in the prevention and treatment of vitamin E deficiencies in swine, cattle and sheep. This product is intended as a supplemental source of natural vitamin E.
Natural tocopherols in feedstuffs can be destroyed through processing, ensiling, and storage. A reduced vitamin E intake can result in marginal deficiencies that may not be visible. Intermuscular or subcutaneous injections offer an efficient and rapid method to increase the vitamin E status of animals.

Each mL contains:

ACTIVE INGREDIENTS: 300 I.U. of vitamin E (as d-alpha-tocopherol, a natural source of vitamin

INACTIVE INGREDIENTS: 2% benzyl alcohol (preservative) in a water emulsifiable base.

Warnings:

Do not add water to this solution. Not for human use. Keep out of reach of children.

STORAGE AND HANDLING

Store between 15° and 30°C (59°-86°F) in a dark place.

CAUTION:

Do not exceed recommended dosage. Occasionally, reactions of an anaphylactic or allergic nature may occur. Should such reactions occur, treat immediately with injection of epinephrine or antihistamines.